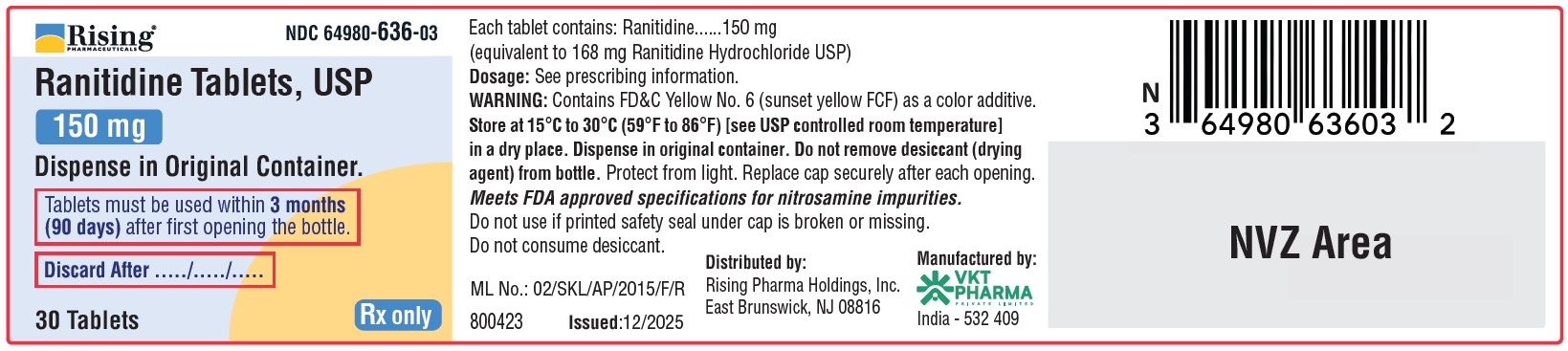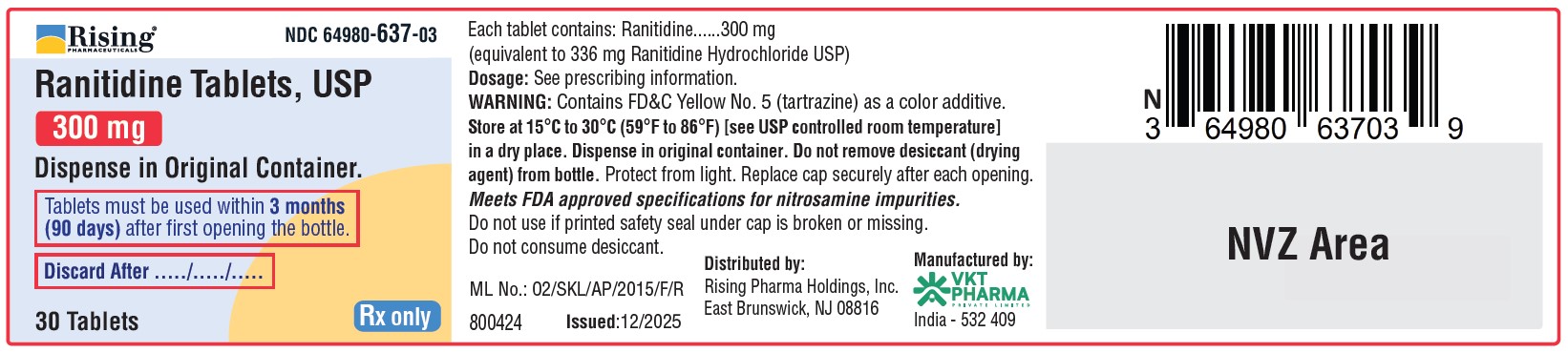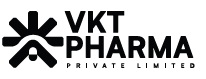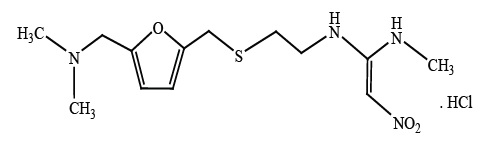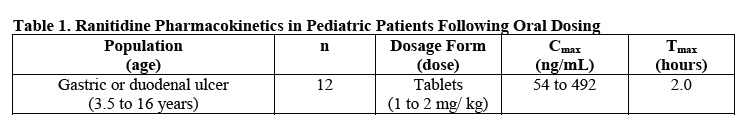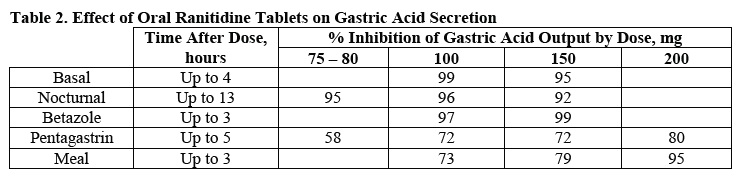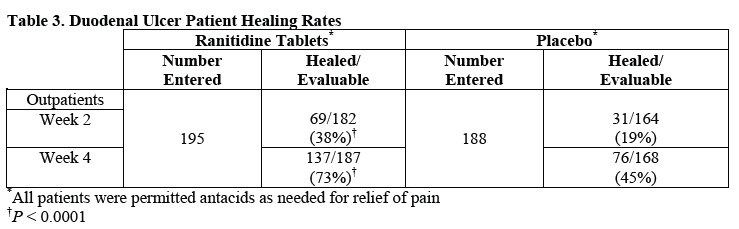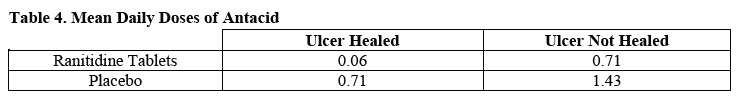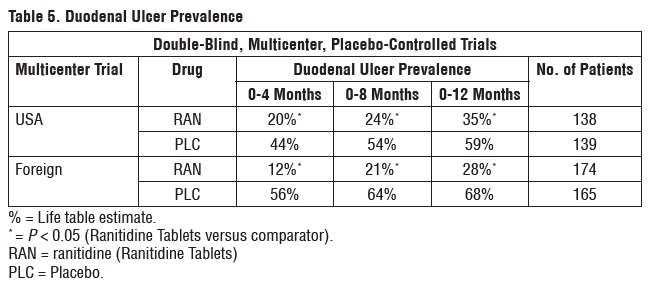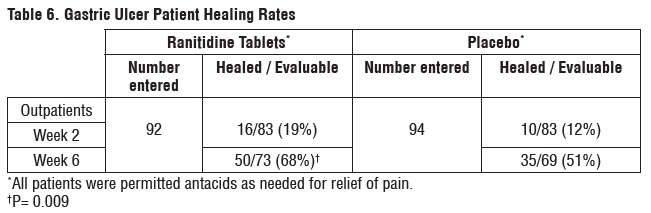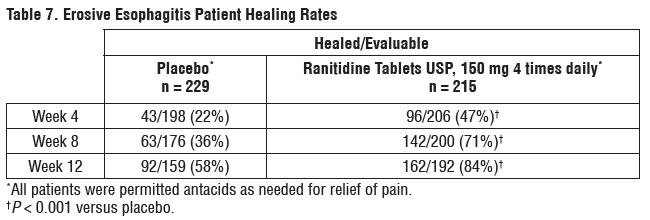 DRUG LABEL: RANITIDINE
NDC: 64980-636 | Form: TABLET
Manufacturer: Rising Pharma Holdings, Inc.
Category: prescription | Type: HUMAN PRESCRIPTION DRUG LABEL
Date: 20251205

ACTIVE INGREDIENTS: RANITIDINE HYDROCHLORIDE 150 mg/1 1
INACTIVE INGREDIENTS: CELLULOSE, MICROCRYSTALLINE; CROSCARMELLOSE SODIUM; MAGNESIUM STEARATE; POLYVINYL ALCOHOL; TALC; TITANIUM DIOXIDE; GLYCERYL MONOSTEARATE; SODIUM LAURYL SULFATE; FD&C YELLOW NO. 6; FERRIC OXIDE YELLOW; WATER

PRESCRIBING INFORMATION
RANITIDINE TABLETS USP 150 mg and 300 mg

DESCRIPTION

Ranitidine Tablets USP are available for oral administration containing 150 mg or 300 mg of ranitidine. The active ingredient in Ranitidine Tablets USP, 150 mg and 300 mg is Ranitidine hydrochloride (HCl), USP, a histamine H2-receptor antagonist.

Chemically it is N[2-[[[5-[(dimethylamino)methyl]-2-furanyl] methyl]thio]ethyl]-N´-methyl-2-nitro-1,1-ethenediamine, HCl. It has the following structure:

The emperical formula is C13H22N4O3S•HCl, representing a molecular weight of 350.87.

Ranitidine HCl is white to pale yellow, crystalline, practically odorless powder, sensitive to light and moisture. Melts at about 140°C with decomposition.

Ranitidine is available as 150 mg and 300 mg tablets for oral administration.

Each Ranitidine Tablet USP, 150 mg contains 150 mg ranitidine (equivalent to 168 mg of ranitidine HCl) and the following inactive ingredients microcrystalline cellulose, croscarmellose sodium, magnesium stearate, Opadry® 200 Orange 203A530006 (Polyvinyl alcohol, talc, titanium dioxide, glycerol monostearate, sodium lauryl sulphate, FD&C yellow 6 and iron oxide yellow), purified water.

Each Ranitidine Tablet USP, 300 mg contains 300 mg ranitidine (equivalent to 336 mg of ranitidine HCl) and the following inactive ingredients microcrystalline cellulose, croscarmellose sodium, magnesium stearate, Opadry® 200 Yellow 203A520014 (Polyvinyl alcohol, talc, titanium dioxide, glycerol monostearate, sodium lauryl sulphate, FD&C yellow 5 and FD&C Blue 1), purified water.

Contains color additives including FD&C Yellow No.5 (tartrazine)

Meets FDA approved specifications for nitrosamine impurities.

CLINICAL PHARMACOLOGY

Ranitidine Tablets are a competitive, reversible inhibitor of the action of histamine at the histamine H2-receptors, including receptors on the gastric cells. Ranitidine Tablets do not lower serum Ca++ in hypercalcemic states. Ranitidine Tablets are not an anticholinergic agent.

Pharmacokinetics

Absorption: Ranitidine Tablets are 50% absorbed after oral administration, compared to an intravenous (IV) injection with mean peak levels of 440 to 545 ng/mL occurring 2 to 3 hours after a 150 mg dose. Absorption is not significantly impaired by the administration of food or antacids. Propantheline slightly delays and increases peak blood levels of ranitidine, probably by delaying gastric emptying and transit time. In one study, simultaneous administration of high-potency antacid (150 mmol) in fasting subjects has been reported to decrease the absorption of Ranitidine Tablets.
Distribution: The volume of distribution is about 1.4 L/kg. Serum protein binding averages 15%.
Metabolism: In humans, the N-oxide is the principal metabolite in the urine; however, this amounts to < 4% of the dose. Other metabolites are the S-oxide (1%) and the desmethyl ranitidine (1%). The remainder of the administered dose is found in the stool. Studies in patients with hepatic dysfunction (compensated cirrhosis) indicate that there are minor, but clinically insignificant, alterations in ranitidine half-life, distribution, clearance, and bioavailability.
Excretion: The principal route of excretion is the urine, with approximately 30% of the orally administered dose collected in the urine as unchanged drug in 24 hours. Renal clearance is about 410 mL/min, indicating active tubular excretion. The elimination half-life is 2.5 to 3 hours. Four patients with clinically significant renal function impairment (creatinine clearance 25 to 35 mL/min) administered 50 mg of ranitidine intravenously had an average plasma half-life of 4.8 hours, a ranitidine clearance of 29 mL/min, and a volume of distribution of 1.76 L/kg. In general, these parameters appear to be altered in proportion to creatinine clearance (see DOSAGE AND ADMINISTRATION).
Geriatrics: The plasma half-life is prolonged and total clearance is reduced in the elderly population due to a decrease in renal function. The elimination half-life is 3 to 4 hours. Peak levels average 526 ng/mL following a 150-mg twice-daily dose and occur in about 3 hours (see PRECAUTIONS: Geriatric Use and DOSAGE AND ADMINISTRATION: Dosage Adjustment for Patients with Impaired Renal Function).
Pediatrics: There are no significant differences in the pharmacokinetic parameter values for ranitidine in pediatric patients (from one month up to 16 yrs of age) and healthy adults when correction is made for body weight. The average bioavailability of Ranitidine is given orally to pediatric patients is 48%, which is comparable to the bioavailability of Ranitidine in the adult population. All other pharmacokinetic parameter values (t1/2, Vd, and CL) are similar to those observed with intravenous Ranitidine use in pediatric patients. Estimates of Cmax and Tmax are displayed in Table 1.

Plasma clearance measured in 2 neonatal patients (less than 1 month of age) was considerably lower (3 mL/min/kg) than children or adults and is likely due to reduced renal function observed in this population (see PRECAUTIONS: Pediatric Use and DOSAGE AND ADMINISTRATION: Pediatric Use).

Pharmacodynamics: Serum concentrations necessary to inhibit 50% of stimulated gastric acid secretion are estimated to be 36 to 94 ng/mL. Following a single oral dose of 150 mg, serum concentrations of Ranitidine are in this range up to 12 hours. However, blood levels bear no consistent relationship to dose or degree of acid inhibition.
Antisecretory Activity:

1. Effects on Acid Secretion: Ranitidine Tablets inhibits both daytime and nocturnal basal gastric acid secretions as well as gastric acid secretion stimulated by food, betazole, and pentagastrin, as shown in below Table 2.

It appears that basal-, nocturnal-, and betazole-stimulated secretions are most sensitive to inhibition by Ranitidine Tablets, responding almost completely to doses of 100 mg or less, while pentagastrin- and food-stimulated secretions are more difficult to suppress.
2. Effects on Other Gastrointestinal Secretions:
Pepsin: Oral Ranitidine Tablets do not affect pepsin secretion. Total pepsin output is reduced in proportion to the decrease in volume of gastric juice.
Intrinsic Factor: Oral Ranitidine Tablets have no significant effect on pentagastrin-stimulated intrinsic factor secretion.
Serum Gastrin: Ranitidine Tablets have little or no effect on fasting or postprandial serum gastrin.

Other Pharmacologic Actions:

1. Gastric bacterial flora - increase in nitrate-reducing organisms, significance not known.
2. Prolactin levels - no effect in recommended oral or IV dosage, but small, transient, dose-related increases in serum prolactin have been reported after IV bolus injections of 100 mg or more.
3. Other pituitary hormones - no effect on serum gonadotropins, TSH, or GH. Possible impairment of vasopressin release.
4. No change in cortisol, aldosterone, androgen, or estrogen levels.
5. No antiandrogenic action.
6. No effect on count, motility, or morphology of sperm.

Pediatrics: Oral doses of 6 to 10 mg/kg/day in 2 or 3 divided doses maintain gastric pH >4 throughout most of the dosing interval.
Clinical Trials: Active Duodenal Ulcer: In a multicenter, double-blind, controlled, US study of endoscopically diagnosed duodenal ulcers, earlier healing was seen in the patients treated with Ranitidine Tablets as shown in Table 3.

In these studies, patients treated with Ranitidine Tablets reported a reduction in both daytime and nocturnal pain, and they also consumed less antacid than the placebo-treated patients.

Foreign studies have shown that patients heal equally well with 150 mg twice daily and 300 mg at bed time (85% versus 84%, respectively) during a usual 4-week course of therapy. If patients require extended therapy of 8 weeks, the healing rate may be higher for 150 mg twice daily as compared to 300 mg at bed time (92% versus 87%, respectively).
Studies have been limited to short-term treatment of acute duodenal ulcer. Patients whose ulcers healed during therapy had recurrences of ulcers at the usual rates.
Maintenance Therapy in Duodenal Ulcer: Ranitidine has been found to be effective as a maintenance therapy for patients, following healing of acute duodenal ulcers. In 2 independent, double-blind, multi-center, controlled trials, the number of duodenal ulcers observed was significantly less in patients treated with Ranitidine Tablets (150 mg at bed time) than in patients treated with placebo over a 12-month period.

As with other H2-antagonists, the factors responsible for the significant reduction in the prevalence of duodenal ulcers include prevention of recurrence of ulcers, more rapid healing of ulcers that may occur during maintenance therapy, or both.
Gastric Ulcer: In a multicenter, double-blind, controlled, US study of endoscopically diagnosed gastric ulcers, earlier healing was seen in the patients treated with Ranitidine Tablets as shown in Table 6.

In this multicenter trial, significantly more patients treated with Ranitidine Tablets became painfree during therapy.
Maintenance of Healing of Gastric Ulcers: In 2 multicenter, double-blind, randomized, placebo-controlled, 12-month trials conducted in patients whose gastric ulcers had been previously healed, Ranitidine Tablets 150 mg at bed time was significantly more effective than placebo in maintaining healing of gastric ulcers.
Pathological Hypersecretory Conditions (such as Zollinger-Ellison syndrome): Ranitidine Tablets inhibits gastric acid secretion and reduces occurrence of diarrhea, anorexia, and pain in patients with pathological hypersecretion associated with Zollinger-Ellison syndrome, systemic mastocytosis, and other pathological hypersecretory conditions. (e.g., postoperative, “short-gut” syndrome, idiopathic). Use of Ranitidine Tablets was followed by healing of ulcers in 8 of 19 (42%) patients who were intractable to previous therapy.
Gastroesophageal Reflux Disease (GERD): In 2 multicenter, double-blind, placebo-controlled, 6-week trials performed in the United States and Europe, Ranitidine Tablets USP, 150 mg twice daily was more effective than placebo for the relief of heartburn and other symptoms associated with GERD. Ranitidine-treated patients consumed significantly less antacid than did placebo-treated patients.
The US trial indicated that Ranitidine Tablets USP, 150 mg twice daily significantly reduced the frequency of heartburn attacks and severity of heartburn pain within 1 to 2 weeks after starting therapy. The improvement was maintained throughout the 6-week trial period. Moreover, patient response rates demonstrated that the effect of heartburn extends through both the day and nighttime periods.
In 2 additional US multicenter, double-blind, placebo-controlled, 2-week trials, Ranitidine Tablets USP, 150 mg twice daily was shown to provide relief of heartburn pain within 24 hours of initiating therapy and a reduction in the frequency of severity of heartburn.
Erosive Esophagitis: In 2 multicenter, double-blind, randomized, placebo-controlled, 12- week trials performed in the United States, Ranitidine Tablets USP, 150 mg 4 times daily was significantly more effective than placebo in healing endoscopically diagnosed erosive esophagitis and in relieving associated heartburn. The erosive esophagitis healing rates were as follows in Table 7:

No additional benefit in healing of esophagitis or in relief of heartburn was seen with a ranitidine dose of 300 mg 4 times daily.

Maintenance of Healing of Erosive Esophagitis: In 2 multicenter, double-blind, randomized, placebo-controlled, 48-week trials conducted in patients whose erosive esophagitis had been previously healed, Ranitidine Tablets USP, 150 mg twice daily was significantly more effective than placebo in maintaining healing of erosive esophagitis.

INDICATIONS AND USAGE

Ranitidine Tablets are indicated in:

1. Short- term treatment of active duodenal ulcer. Most patients heal within 4 weeks. Studies available to date have not assessed the safety of Ranitidine in uncomplicated duodenal ulcer for periods of more than 8 weeks.
2. Maintenance therapy for duodenal ulcer patients at reduced dosage after healing of acute ulcers. No placebo- controlled comparative studies have been carried out for periods of longer than 1 year.
3. The treatment of pathological hypersecretory conditions (e.g., Zollinger-Ellison syndrome and systemic mastocytosis).
4. Short-term treatment of active, benign gastric ulcers. Most patients heal within 6 weeks and the usefulness of further treatment has not been demonstrated. Studies available to date have not assessed the safety of ranitidine in uncomplicated, benign gastric ulcer for periods of more than 6 weeks.
5. Maintenance therapy for gastric ulcer patients at reduced dosage after healing of acute ulcers. Placebo-controlled studies have been carried out for 1 year.
6. Treatment of GERD. Symptomatic relief commonly occurs within 24 hours after starting therapy with Ranitidine Tablets USP, 150 mg twice daily.
7. Treatment of endoscopically diagnosed erosive esophagitis. Symptomatic relief of heartburn commonly occurs within 24 hours of therapy initiation with Ranitidine Tablets USP, 150 mg 4 times daily.
8. Maintenance of healing of erosive esophagitis. Placebo-controlled trials have been carried out for 48 weeks.

Concomitant antacids should be given as needed for pain relief to patients with active duodenal ulcer; active, benign gastric ulcer; hypersecretory states; GERD; and erosive esophagitis.

CONTRAINDICATIONS

Ranitidine Tablets are contraindicated for patients known to have hypersensitivity to the drug or any of the ingredients (see PRECAUTIONS).

PRECAUTIONS

General:

1. Symptomatic response to therapy with Ranitidine Tablets does not preclude the presence of gastric malignancy.
2. Since Ranitidine Tablets are excreted primarily by the kidney, dosage should be adjusted in patients with impaired renal function (see DOSAGE AND ADMINISTRATION). Caution should be observed in patients with hepatic dysfunction since Ranitidine Tablets are metabolized in the liver.
3. Rare reports suggest that Ranitidine Tablets may precipitate acute porphyric attacks in patients with acute porphyria. Ranitidine Tablets should therefore be avoided in patients with a history of acute porphyria.
4. This product contains FD&C Yellow No. 5 (tartrazine) which may cause allergic-type reactions (including bronchial asthma) in certain susceptible persons. Although the overall incidence of FD&C Yellow No 5 (tartrazine) sensitivity in the general population is low, it is frequently seen in patients who also have aspirin hypersensitivity.

Laboratory Tests: False-positive tests for urine protein with MULTISTIX® may occur during therapy with Ranitidine Tablets, and therefore testing with sulfosalicylic acid is recommended.
Drug Interactions: Ranitidine has been reported to affect the bioavailability of other drugs through several different mechanisms such as competition for renal tubular secretion, alteration of gastric pH, and inhibition of cytochrome P450 enzymes.
Procainamide: Ranitidine, a substrate of the renal organic cation transport system, may affect the clearance of other drugs eliminated by this route. High doses of ranitidine (e.g., such as those used in the treatment of Zollinger-Ellison syndrome) have been shown to reduce the renal excretion of procainamide and N-acetylprocainamide resulting in increased plasma levels of these drugs. Although this interaction is unlikely to be clinically relevant at usual ranitidine doses, it may prudent to monitor for procainamide toxicity when administered with oral ranitidine at a dose exceeding 300 mg per day.
Warfarin: There have been reports of altered prothrombin time among patients on concomitant warfarin and ranitidine therapy. Due to the narrow therapeutic index, close monitoring of increased or decreased prothrombin time is recommended during concurrent treatment with ranitidine.

Ranitidine may alter the absorption of drugs in which gastric pH is an important determinant of bio-availability. This can result in either an increase in absorption (e.g., triazolam, midazolam, glipizide) or a decrease in absorption (e.g., ketoconazole, Atazanavir, delavirdine, gefitinib). Appropriate clinical monitoring is recommended.
Atazanavir: Atazanavir absorption may be impaired based on known interactions with other agents that increase gastric pH. Use with caution. See atazanavir label for specific recommendations.
Delavirdine: Delavirdine absorption may be impaired based on known interactions with other agents that increase gastric pH. Chronic use of H2-receptor antagonists with delavirdine is not recommended.
Gefitinib: Gefitinib exposure was reduced by 44% with the co-administration of ranitidine and sodium bicarbonate (dosed to maintain gastric pH above 5.0). Use with caution.
Glipizide: In diabetic patients, glipizide exposure was increased by 34% following a single 150 mg dose of oral ranitidine. Use appropriate clinical monitoring when initiating or discontinuing ranitidine.
Ketoconazole: Oral ketoconazole exposure was reduced by up to 95% when oral ranitidine was co-administered in a regimen to maintain a gastric pH of 6 or above. The degree of interaction with usual dose of ranitidine (150 mg twice daily) is unknown.
Midazolam: Oral midazolam exposure in 5 healthy volunteers was increased by up to 65% when administered with oral ranitidine at a dose of 150 mg twice daily. However, in another interaction trail in 8 volunteers receiving IV midazolam, a 300 mg oral dose of ranitidine increased midazolam exposure by about 9%. Monitor patients for excessive or prolonged sedation when ranitidine is co-administered with oral midazolam.
Triazolam: Triazolam exposure in healthy volunteers was increased by approximately 30% when administered with oral ranitidine at a dose of 150 mg twice daily. Monitor patients for excessive or prolonged sedation.
Carcinogenesis, Mutagenesis, and Impairment of Fertility: There was no indication of tumorigenic or carcinogenic effects in life-span studies in mice and rats at dosages up to 2,000 mg/kg/day.

Ranitidine was not mutagenic in standard bacterial tests (Salmonella, Escherichia coli) for mutagenecity at concentrations up to the maximum recommended for these assays.

In a dominant lethal assay, a single oral dose of 1,000 mg/kg to male rats was without effect on the outcome of 2 matings per week for the next 9 weeks.

Information for Patients:

- Keep Ranitidine Tablets in the original container (bottle) and protect from moisture.
- After the first opening of the bottle, discard unused tablets after 3 months (90 days), or by the expiration date on the bottle, whichever is sooner.
- If more than one bottle is dispensed, open only one bottle at a time. Store additional bottles without opening until needed for dosing.
- At the time of dosing, remove one tablet from the bottle. Immediately close the bottle, secure the cap, and keep the bottle tightly closed.
- Keep the desiccant in the bottle.

Pregnancy:

Teratogenic Effects: Reproduction studies have been performed in rats and rabbits at doses up to 160 times the human dose and have revealed no evidence of impaired fertility or harm to the fetus due to Ranitidine Tablets. There are, however, no adequate and well-controlled studies in pregnant women. Because animal reproduction studies are not always predictive of human response, this drug should be used during pregnancy only if clearly needed.
Nursing Mothers: Ranitidine is secreted in human milk. Caution should be exercised when Ranitidine Tablets are administered to a nursing mother.
Pediatric Use: The safety and effectiveness of Ranitidine Tablets have been established in the age-group of 1 month to 16 years for the treatment of duodenal and gastric ulcers, gastroesophageal reflux disease and erosive esophagitis, and the maintenance of healed duodenal and gastric ulcer. Use of Ranitidine Tablets in this age group is supported by adequate and well-controlled studies in adults, as well as additional pharmacokinetic data in pediatric patients and an analysis of the published literature (see CLINICAL PHARMACOLOGY: Pediatrics and DOSAGE AND ADMINISTRATION: Pediatric Use).

Safety and effectiveness in pediatric patients for the treatment of pathological hypersecretory conditions or the maintenance of healing of erosive esophagitis have not been established.

Safety and effectiveness in neonates (less than 1 month of age) have not been established (see CLINICAL PHARMACOLOGY: Pediatrics).
Geriatric Use: Of the total number of subjects enrolled in US and foreign controlled clinical trials of oral formulations of ranitidine for which there were subgroup analyses, 4,197 were 65 and over, while 899 were 75 and over. No overall differences in safety or effectiveness were observed between these subjects and younger subjects, and other reported clinical experience has not identified differences in responses between the elderly and younger patients, but greater sensitivity of some older individuals cannot be ruled out.

This drug is known to be substantially excreted by the kidney and the risk of toxic reactions to this drug may be greater in patients with impaired renal function. Because elderly patients are more likely to have decreased renal function, caution should be exercised in dose selection, and it may be useful to monitor renal function. (See CLINICAL PHARMACOLOGY: Pharmacokinetics: Geriatrics and DOSAGE AND ADMINISTRATION: Dosage Adjustment for Patients with Impaired Renal Function).

ADVERSE REACTIONS

The following have been reported as events in clinical trials or in the routine management of patients treated with Ranitidine Tablets. The relationship to therapy with Ranitidine Tablets has been unclear in many cases. Headache, sometimes severe, seems to be related to administration of Ranitidine Tablets.
Central Nervous System: Rarely, malaise, dizziness, somnolence, insomnia, and vertigo. Rare cases of reversible mental confusion, agitation, depression, and hallucinations have been reported, predominantly in severely ill elderly patients. Rare cases of reversible blurred vision suggestive of a change in accommodation have been reported. Rare reports of reversible involuntary motor disturbances have been received.
Cardiovascular: As with other H2-blockers, rare reports of arrhythmias such as tachycardia, bradycardia, atrioventricular block, and premature ventricular beats.
Gastrointestinal: Constipation, diarrhea, nausea/vomiting, abdominal discomfort/pain, and rare reports of pancreatitis.
Hepatic: There have been occasional reports of hepatocellular, cholestatic, or mixed hepatitis, with or without jaundice. In such circumstances, ranitidine should be immediately discontinued. These events are usually reversible, but in rare circumstances death has occurred. Rare cases of hepatic failure have also been reported. In normal volunteers, SGPT values were increased to at least twice the pretreatment levels in 6 of 12 subjects receiving 100 mg intravenously 4 times daily for 7 days, and in 4 of 24 subjects receiving 50 mg intravenously 4 times daily for 5 days.
Musculoskeletal: Rare reports of arthralgias and myalgias.
Hematologic: Blood count changes (leukopenia, granulocytopenia, and thrombocytopenia) have occurred in a few patients. These were usually reversible. Rare cases of agranulocytosis, pancytopenia, sometimes with narrow hypoplasia, and aplastic anemia and exceedingly rare cases of acquired immune hemolytic anemia have been reported.
Endocrine: Controlled studies in animals and man have shown no stimulation of any pituitary hormone by Ranitidine Tablets and no antiadrenogenic activity, and cimetidine-induced gynecomastia and impotence in hypersecretory patients have resolved when Ranitidine Tablets has been substituted.
However, occasional cases of impotence and loss of libido have been reported in male patients receiving Ranitidine Tablets, but the incidence did not differ from that in the general population. Rare cases of breast symptoms and conditions, including galactorrhea and gynecomastia, have been reported in both males and females.
Integumentary: Rash, including rare cases of erythema multiforme. Rare cases of alopecia and vasculitis.
Respiratory: A large epidemiological study suggested an increased risk of developing pneumonia in current users of histamine-2-receptor antagonists (H2RAs) compared with patients who had stopped H2RA treatment, with an observed adjusted relative risk of 1.63 (95% CI, 1.07-2.48). However, a causal relationship between use of H2RAs and pneumonia has not been established.
Other: Rare cases of hypersensitivity reactions (e.g., bronchospasm, fever, rash, eosinophilia), anaphylaxis, angioneurotic edema, acute interstitial nephritis, and small increases in serum creatinine.

To report SUSPECTED ADVERSE REACTIONS, contact Rising Pharma Holdings, Inc. at 1-844-874-7464 or FDA at 1-800-FDA-1088 or www.fda.gov/medwatch.

OVERDOSAGE

There has been limited experience with overdosage. Reported acute ingestions of up to 18 g orally have been associated with transient adverse effects similar to those encountered in normal clinical experience (see ADVERSE REACTIONS). In addition, abnormalities of gait and hypotension have been reported.
When overdosage occurs, the usual measures to remove unabsorbed material from the gastrointestinal tract, clinical monitoring, and supportive therapy should be employed.
Studies in dogs receiving dosages of Ranitidine, in excess of 225 mg/kg/day have shown muscular tremors, vomiting, and rapid respiration. Single oral doses of 1,000 mg/kg in mice and rats were not lethal. Intravenous LD50, values in mice and rats were 77 and 83 mg/kg, respectively.

DOSAGE AND ADMINISTRATION

Active Duodenal Ulcer: The current recommended adult oral dosage of Ranitidine Tablets for duodenal ulcer is 150 mg twice daily. An alternative dosage of 300 mg once daily after the evening meal or at bedtime can be used for patients in whom dosing convenience is important. The advantages of one treatment regimen compared with the other in a particular patient population have yet to be demonstrated (see Clinical Trials: Active Duodenal Ulcer). Smaller doses have been shown to be equally effective in inhibiting gastric acid secretion in US studies, and several foreign trials have shown that 100 mg twice daily is as effective as the 150 mg dose.
Antacid should be given as needed for relief of pain (see CLINICAL PHARMACOLOGY: Pharmacokinetics).
Maintenance of Healing of Duodenal Ulcers: The current recommended adult oral dosage is 150 mg at bedtime.
Pathological Hypersecretory Conditions (such as Zollinger - Ellison syndrome): The current recommended adult oral dosage is 150 mg twice daily. In some patients it may be necessary to administer Ranitidine Tablets USP, 150 mg doses more frequently. Dosages should be adjusted to individual patient needs, and should continue as long as clinically indicated. Dosages up to 6 g/day have been employed in patients with severe disease.
Benign Gastric Ulcer: The current recommended adult oral dosage is 150 mg twice daily.
Maintenance of Healing of Gastric Ulcers: The current recommended adult oral dosage is 150 mg at bedtime.
GERD: The current recommended adult oral dosage is 150 mg twice daily.
Erosive Esophagitis: The current recommended adult oral dosage is 150 mg 4 times daily.
Maintenance of Healing of Erosive Esophagitis: The current recommended adult oral dosage is 150 mg twice daily.
Pediatric Use: The safety and effectiveness of Ranitidine Tablets have been established in the age group of 1 month to 16 years. There is insufficient information about the pharmacokinetics of Ranitidine Tablets in neonatal patients (less than 1 month of age) to make dosing recommendations.
The following 3 subsections provide dosing information for each of the pediatric indications.
Treatment of Duodenal and Gastric Ulcers: The recommended oral dose for the treatment of active duodenal and gastric ulcers is 2 to 4 mg/kg twice daily to a maximum of 300 mg/day. This recommendations is derived from adult clinical studies and pharmacokinetic data in pediatric patients.
Maintenance of Healing of Duodenal and Gastric Ulcers: The recommended oral dose for the maintenance of healing of duodenal and gastric ulcers is to 2 to 4 mg/kg once daily to a maximum of 150 mg/day. This recommendation is derived from adult clinical studies and pharmacokinetic data in pediatric patients.
Treatment of GERD and Erosive Esophagitis: Although limited data exist for these conditions in pediatric patients, published literature supports a dosage of 5 to 10 mg/kg/day, usually given as 2 divided doses.
Dosage Adjustment for Patients with Impaired Renal Function: On the basis of experience with a group of subjects with severely impaired renal function treated with Ranitidine Tablets, the recommended dosage in patients with a creatinine clearance < 50 mL/min is 150 mg every 24 hours. Should the patient’s condition require, the frequency of dosing may be increased to every 12 hours or even further with caution. Hemodialysis reduces the level of circulating ranitidine. Ideally, the dosing schedule should be adjusted so that the timing of a scheduled dose coincides with the end of hemodialysis.
Elderly patients are more likely to have decreased renal function, therefore caution should be exercised in dose selection, and it may be useful to monitor renal function (see CLINICAL PHARMACOLOGY: Pharmacokinetics: Geriatrics and PRECAUTIONS : Geriatric Use).

HOW SUPPLIED

Ranitidine Tablets USP, 150 mg (Ranitidine HCl equivalent to 150 mg of ranitidine) are orange, round shaped tablets debossed with ‘V’ on one side and ‘37’ on the other side.
They are available in following count

- Bottles of 30 tablets (NDC 64980-636-03)

Ranitidine Tablets USP, 300 mg (Ranitidine HCl equivalent to 300 mg of ranitidine) are yellow, oval shaped tablets debossed with ‘V’ on one side and ‘03’ on the other side.
They are available in following count

- Bottles of 30 tablets (NDC 64980-637-03)

Contains color additives including FD&C Yellow No.5 (tartrazine)

Storage: Store at 15ºC to 30ºC (59ºF to 86ºF) [see USP controlled room temperature] in a dry place.

Dispense in the original container.

Note to the Pharmacist: Inform the patient after first opening, store the tablets in the original bottle for up to 3 months (90 days). If the tablets are not used within 3 months (90 days), discard unused tablets. The discard after date should be noted on the bottle.

- Replace cap securely after each opening. Keep the bottle tightly closed.
- Do not remove desiccant from bottle.
- Protect from light.

*MULTISTIX is a registered trademark of Bayer Healthcare LLC.

Distributed by:
Rising Pharma Holdings, Inc.
East Brunswick, NJ 08816

Manufactured by:

VKT Pharma Private Limited

Srikakulam District, India-532-409

Issued: 12/2025

800425

PACKAGE LABEL

Rising®
PHARMACEUTICALS
NDC 64980-636-03
Ranitidine Tablets USP, 150 mg
30 Tablets Rx only

PACKAGE LABEL

Rising®
PHARMACEUTICALS
NDC 64980-637-03
Ranitidine Tablets USP, 300 mg
30 Tablets Rx only